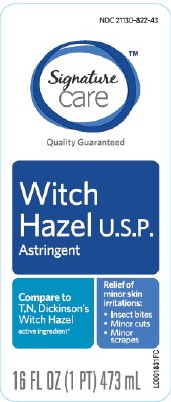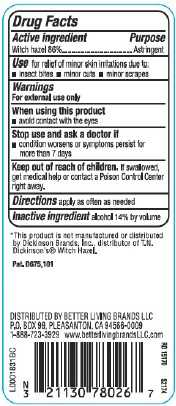 DRUG LABEL: Witch Hazel
NDC: 21130-822 | Form: LIQUID
Manufacturer: Better Living Brands, LLC
Category: otc | Type: HUMAN OTC DRUG LABEL
Date: 20260224

ACTIVE INGREDIENTS: WITCH HAZEL 860 mg/1 mL
INACTIVE INGREDIENTS: ALCOHOL

Signature Care 822.001/822AA
Witch Hazel

Active ingredient

Witch Hazel 86%

Purpose

Astringent

Use

for relief of minor skin irritations due to:

- insect bites
- minor cuts
- minor scrapes

Warnings

For external use only

When using this product

avoid contact with the eyes

Stop use and ask a doctor if

- condition worsens or symptoms persist for more than 7 days

Keep out of reach of children.

If swallowed, get medical help or contact a Poison Control Center right away.

Directions

apply as often as needed

Inactive ingredient

alcohol 14% by volume

Disclaimer

*This product is not manufactured or distributed by Dickinson Brands, Inc., distributor of T.N. Dickinson's®Witch Hazel.

ADVERSE REACTION

DISTRIBUTED BY BETTER LIVING BRANDS LLC

P.O. BOX 99, PLEASANTON, CA 94566-009

1-888-723-3929 www.betterlivingbrandsLLC.com

Pat. D675, 101

principal display panel

NDC 21130-822-43

Signature Care™

Quality Guaranteed

Witch Hazel U.S.P.

Astringent

Relief of minor skin irritations:

- Insect bites
- Minor cuts
- Minor scrapes

Compare to T.N. Dickinson's Witch Hazel active ingredient*

16 FL OZ (1 PT) 473 mL